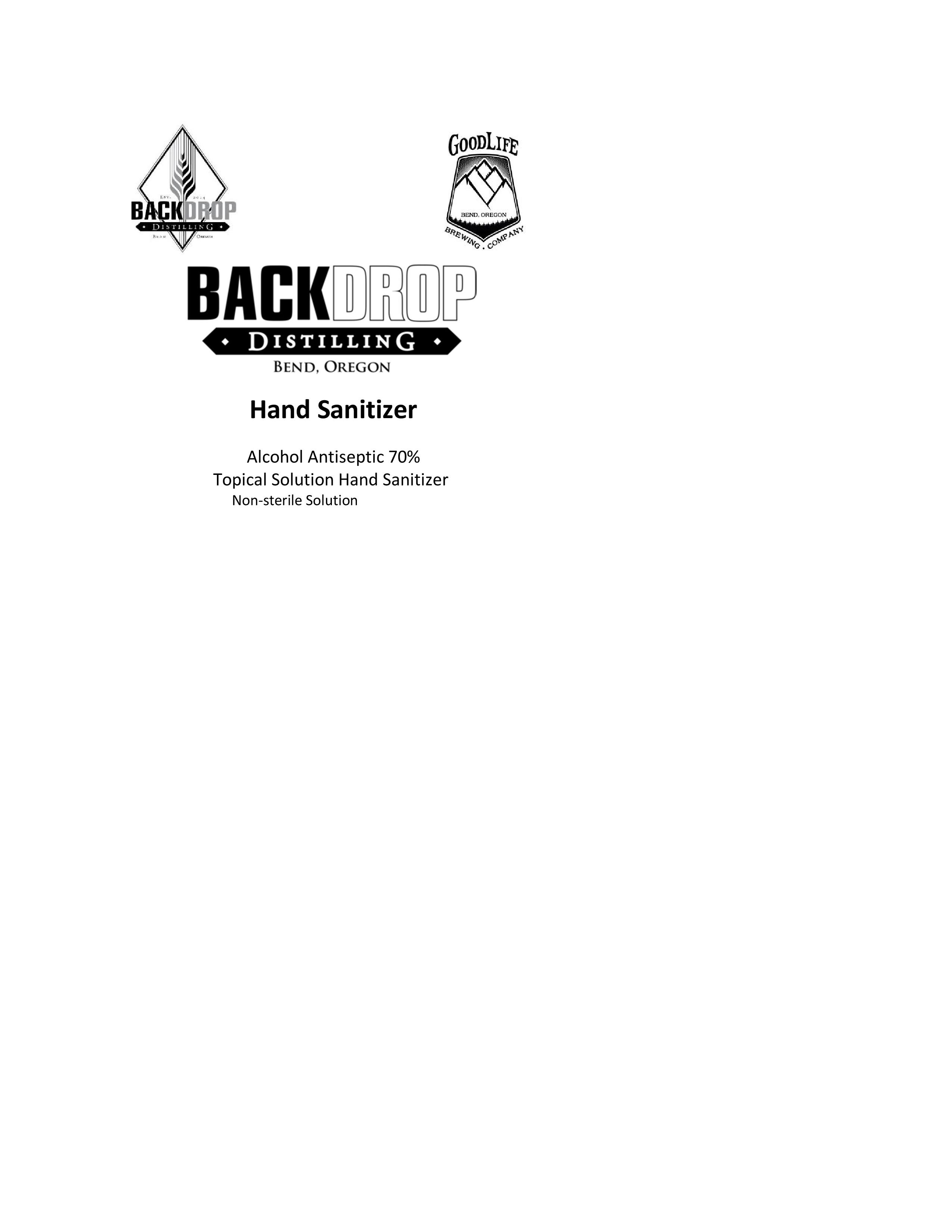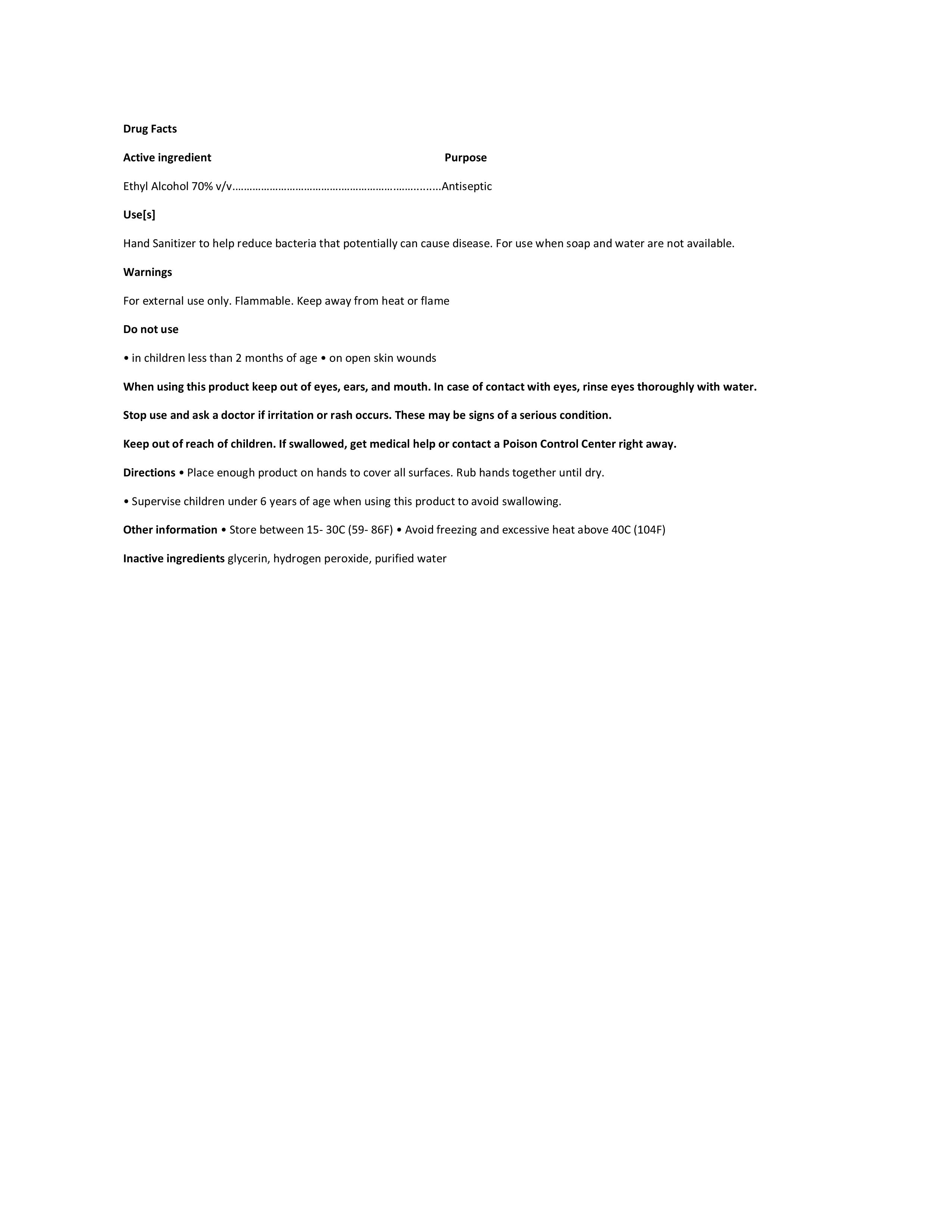 DRUG LABEL: Backdrop Distilling Hand Sanitizer
NDC: 74289-001 | Form: LIQUID
Manufacturer: Backdrop Distilling
Category: otc | Type: HUMAN OTC DRUG LABEL
Date: 20200331

ACTIVE INGREDIENTS: ALCOHOL 1000 mL/1390.025 mL
INACTIVE INGREDIENTS: GLYCEROL FORMAL 19.575 mL/1390.025 mL; HYDROGEN PEROXIDE 56.25 mL/1390.025 mL; WATER 314.2 mL/1390.025 mL

Backdrop Distilling Hand Sanitizer

Active Ingredient and Back Label

Ethyl Alcohol 70% v/v Purpose Antiseptic

Do not use

-in children less than 2 months of age

-on open skin wounds

Keep out of reach of children. If swallowed,

get medical help or contact a Poison Control Center

right away.

Purpose section

Use(s)

Hand Sanitizer to help reduce bacteria that potentially

can casue disease. For use when soap and water are not

available.

Stop use section

Stop use and ask a doctor if irritation or rash occurs.

These may be signs of a serious condition.

When using

When using this product keep out of eyes, ears, and mouth.

In case of contact with eyes, rinse eyes thoroughly

with water.

Other safety

Other information

-Store between 15-30C (59-86F)

-Avoid freezing and excessive heat above 40C (104F)

Warnings

For external use only. Flammable. Keep away from

heat or flame.

Directions

-Place enough product on the hands to cover all surfaces.

Rub hands together until dry.

-Supervise children under 6 years of age when using

this product to avoid swallowing.

Inactive Ingredients

Inactive ingredients glycerin, hydrogen

peroxide, purified water

Dosage

Directions

-Place enough product on hands to cover all surfaces.

Rub hands together until dry.

-Supervise children under 6 years of age when using

this product to avoid swallowing.

Warnings

For external use only. Flammable. Keep away from

heat or flame.

Do not use

-In children less than 2 months of age

-on open skin wounds

When using this product keep out of eyes, ears, and

mouth. In case of contact with eyes, rinse eyes

thoroughly with water.

Stop use and ask a doctor if irritation or rash occurs.

These may be signs of a serious condition.

Keep out of reach of children. If swallowed, get

medical help or contact a Poison Control Center right

away.

Indications and usage

Use(s)

Hand Sanitizer to help reduce bacteria that potentially

cause disease. For use when soap and water are not

available.

Directions

-Place enough product on hands to cover all surfaces.

Rub hands together until dry.

-Supervise children under 6 years of age when using

this product to avoid swallowing.

Front Label

(Logo)

Hand Sanitizer

Alcohol Antiseptic 70%

Topical Solution Hand Santizer

Non-sterile Solution